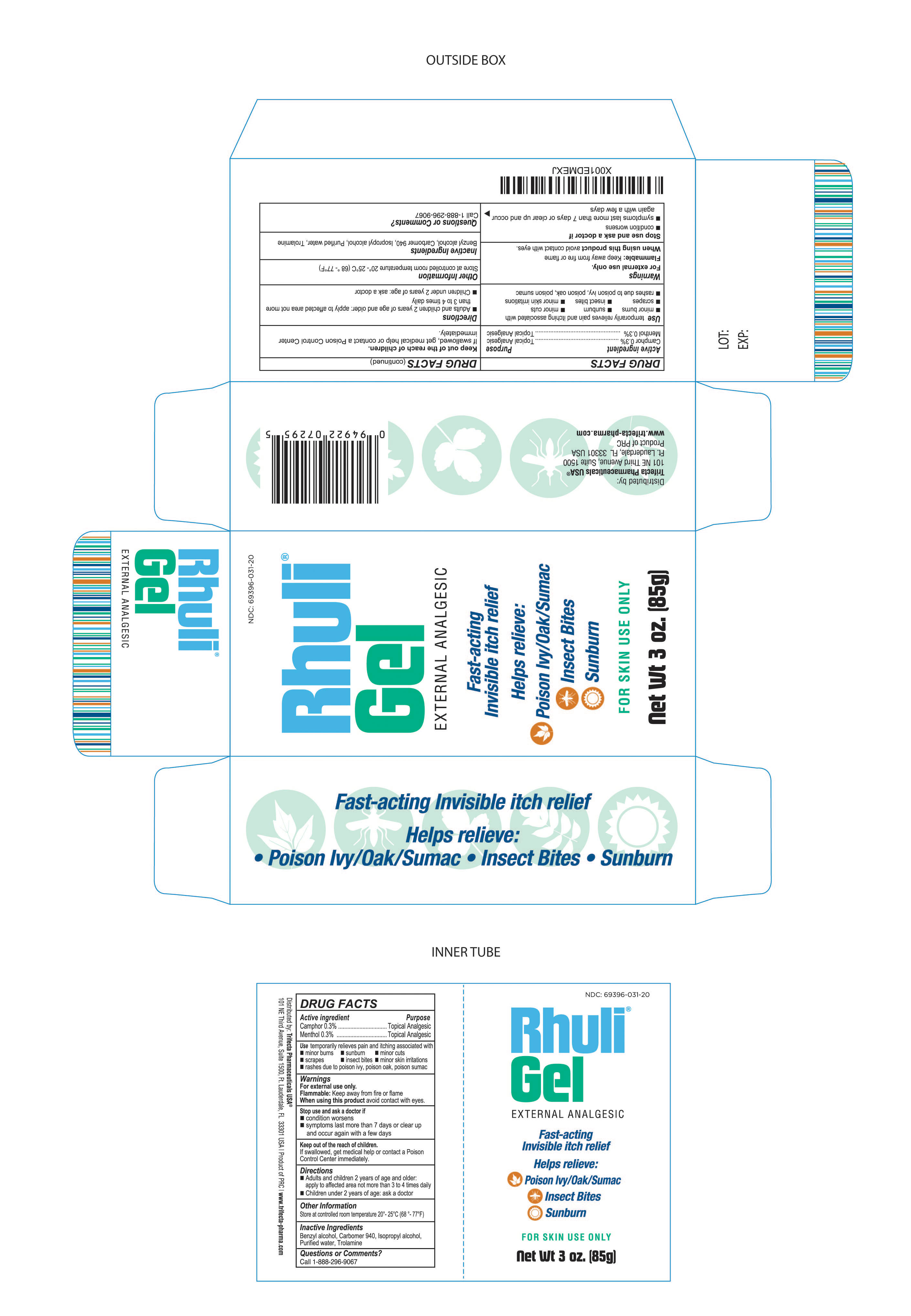 DRUG LABEL: Rhuli Gel
NDC: 69396-031 | Form: GEL
Manufacturer: Trifecta Pharmaceuticals USA, LLC.
Category: otc | Type: HUMAN OTC DRUG LABEL
Date: 20241220

ACTIVE INGREDIENTS: CAMPHOR (SYNTHETIC) 0.3 g/100 g; MENTHOL 0.3 g/100 g
INACTIVE INGREDIENTS: CARBOMER 940; ISOPROPYL ALCOHOL; BENZYL ALCOHOL; WATER; TROLAMINE

Rhuli Gel

Active Ingredient

Camphor 0.3%

Purpose

Topical Analgesic

Active Ingredient

Menthol 0.3%

Purpose

Topical Analgesic

Uses

Temporarily relieves pain and itching associated with:

- minor burns
- scrapes
- sunburn
- insect bites
- minor cuts
- minor skin irritations
- rashes due to poison ivy, poison oak, poison sumac

Warnings

For external use only

Flammable: Keep away from fire or flame

When using this product: avoid contact with eyes

Stop Use and Ask Doctor if:

- Condition worsens
- Symptoms last more than 7 days or clear up and occur again with a few days

Keep out of reach of children

If swallowed, get medical help or contact a Poison Control Center immediately.

Directions:

- Adults and children 2 years of age and older: apply to affected area not more than 3 to 4 times daily.
- Children under 2 years of age: ask a doctor

Other information:

- Store at controlled room temperature 20°-25°C (68°-77°F).
- Close cap tightly after use

Questions: Call 1-888-296-9067

Inactive Ingredients

- Benzyl alcohol, Carbomer 940, Isopropyl alcohol, Purified water, Trolamine

Distributed By:

Trifecta Pharmaceuticals USA, LLC.

101 NE Third Ave. Suite 1500

Ft. Lauderdale, FL. 33301 USA

www.trifecta-pharma.com